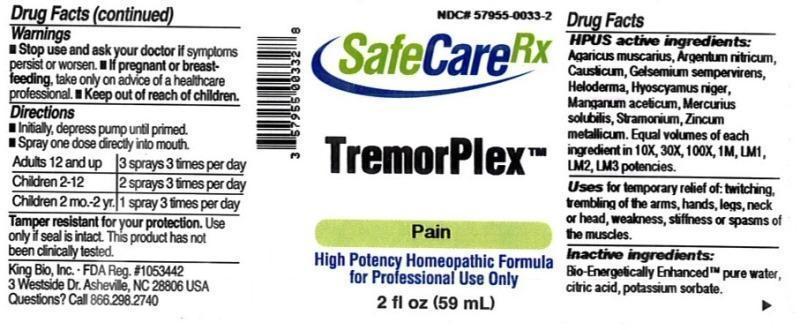 DRUG LABEL: TremorPlex
NDC: 57955-0033 | Form: LIQUID
Manufacturer: King Bio Inc.
Category: homeopathic | Type: HUMAN OTC DRUG LABEL
Date: 20150313

ACTIVE INGREDIENTS: AMANITA MUSCARIA FRUITING BODY 10 [hp_X]/59 mL; SILVER NITRATE 10 [hp_X]/59 mL; CAUSTICUM 10 [hp_X]/59 mL; GELSEMIUM SEMPERVIRENS ROOT 10 [hp_X]/59 mL; HELODERMA HORRIDUM VENOM 10 [hp_X]/59 mL; HYOSCYAMUS NIGER 10 [hp_X]/59 mL; MANGANESE ACETATE TETRAHYDRATE 10 [hp_X]/59 mL; MERCURIUS SOLUBILIS 10 [hp_X]/59 mL; DATURA STRAMONIUM 10 [hp_X]/59 mL; ZINC 10 [hp_X]/59 mL
INACTIVE INGREDIENTS: WATER; ANHYDROUS CITRIC ACID; POTASSIUM SORBATE

TremorPlex™

ACTIVE INGREDIENT

Drug Facts__________________________________________________________________________________________________________

HPUS active ingredients: Agaricus muscarius, Argentum nitricum, Causticum, Gelsemium sempervirens, Heloderma, Hyoscyamus niger, Manganum aceticum, Mercurius solubilis, Stramonium, Zincum metallicum. Equal volumes of each ingredient in 10X, 30X, 100X, 1M, LM1, LM2, LM3 potencies.

INDICATIONS AND USAGE

Uses for temporary relief of: twitching, trembling of the arms, hands, legs, neck or head, weakness, stiffness or spasms of the muscles.

Inactive Ingredients:

Bio-Energetically Enhanced™ pure water, citric acid and potassium sorbate.

Warnings

- Stop use and ask your doctor if symptoms persist or worsen.
- If pregnant or breast-feeding, take only on advice of a healthcare professional.

- Keep out of reach of children.

Directions

- Initially, depress pump until primed.
- Spray one dose directly into mouth.
- Adults 12 and up: 3 sprays 3 times per day
- Children 2-12: 2 sprays 3 times per day
- Children 2mo-2yr.: 1 spray 3 times per day

OTHER SAFETY INFORMATION

Tamper resistant for your protection. Use only if safety seal is intact. This product has not been independently tested.

PURPOSE

Uses for temporary relief of:

- twitching
- trembling of the arms, hands, legs, neck or head
- weakness, stiffness or spasms of the muscles